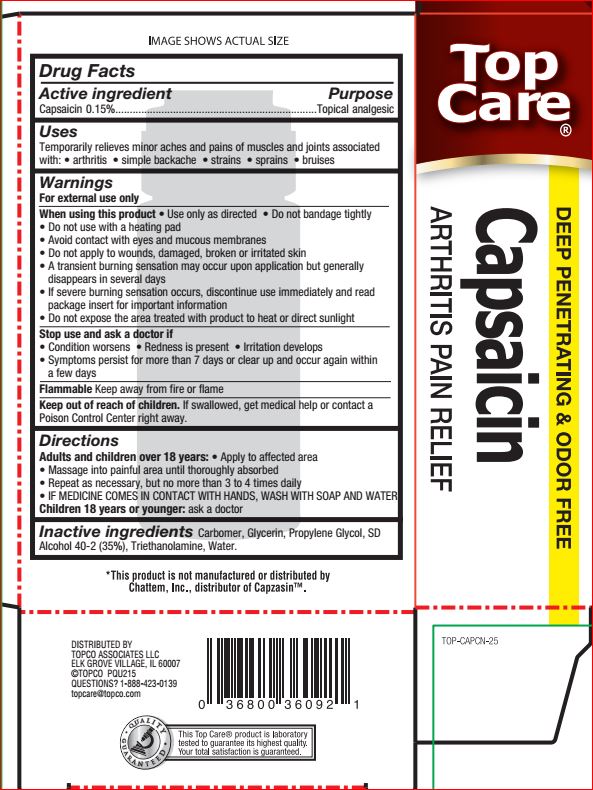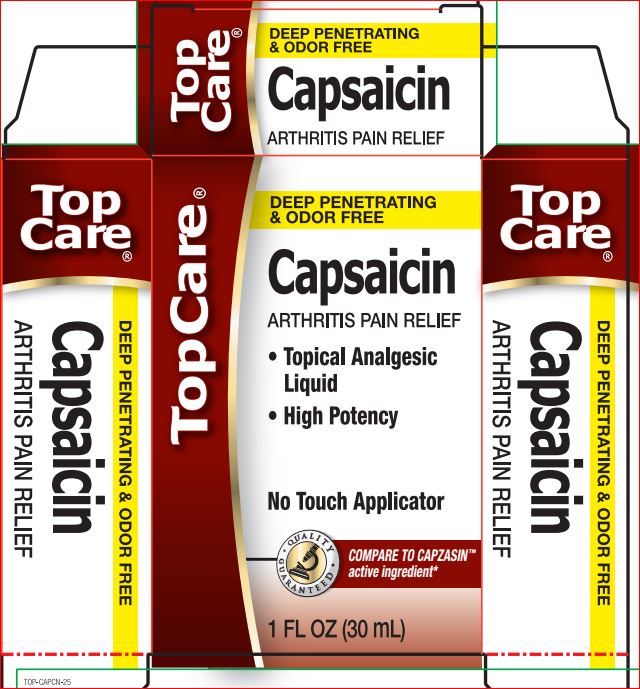 DRUG LABEL: Capsaicin
NDC: 36800-729 | Form: LIQUID
Manufacturer: Top Care
Category: otc | Type: HUMAN OTC DRUG LABEL
Date: 20180718

ACTIVE INGREDIENTS: Capsaicin 0.15 g/100 mL
INACTIVE INGREDIENTS: CARBOMER HOMOPOLYMER TYPE C (ALLYL PENTAERYTHRITOL CROSSLINKED); Glycerin; Propylene Glycol; Alcohol; TROLAMINE; Water

Drug Facts

Active ingredient Purpose
Capsaicin 0.15%......................................................................Topical analgesic

Uses
Temporarily relieves minor aches and pains of muscles and joints associated with: • arthritis • simple backache • strains • sprains • bruises

Warnings
For external use only
When using this product • Use only as directed • Do not bandage tightly
• Do not use with a heating pad
• Avoid contact with eyes and mucous membranes
• Do not apply to wounds, damaged, broken or irritated skin
• A transient burning sensation may occur upon application but generally
disappears in several days
• If severe burning sensation occurs, discontinue use immediately and read
package insert for important information
• Do not expose the area treated with product to heat or direct sunlight
Stop use and ask a doctor if
• Condition worsens • Redness is present • Irritation develops
• Symptoms persist for more than 7 days or clear up and occur again within
a few days
Flammable Keep away from fire or flame

Keep out of reach of children. If swallowed, get medical help or contact a Poison Control Center right away.

Directions
Adults and children over 18 years: • Apply to affected area
• Massage into painful area until thoroughly absorbed
• Repeat as necessary, but no more than 3 to 4 times daily
• IF MEDICINE COMES IN CONTACT WITH HANDS, WASH WITH SOAP AND WATER
Children 18 years or younger: ask a doctor

Inactive ingredients

Carbomer, Glycerin, Propylene Glycol, SD
Alcohol 40-2 (35%), Triethanolamine, Water.